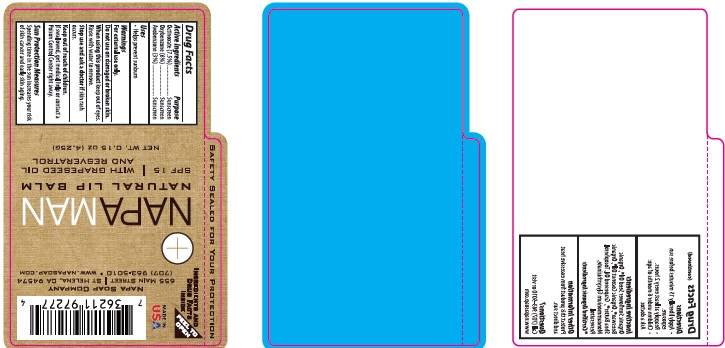 DRUG LABEL: LIP BALM
NDC: 62932-177 | Form: STICK
Manufacturer: Private Label Select Ltd CO
Category: otc | Type: HUMAN OTC DRUG LABEL
Date: 20181117

ACTIVE INGREDIENTS: OCTINOXATE 7.5 g/100 g; OXYBENZONE 6 g/100 g; AVOBENZONE 3 g/100 g
INACTIVE INGREDIENTS: COCONUT OIL; SUNFLOWER OIL; YELLOW WAX; GRAPE SEED OIL; AMMONIUM GLYCYRRHIZATE; RESVERATROL; SHEA BUTTER

Napa Soap Lip Balm SPF15